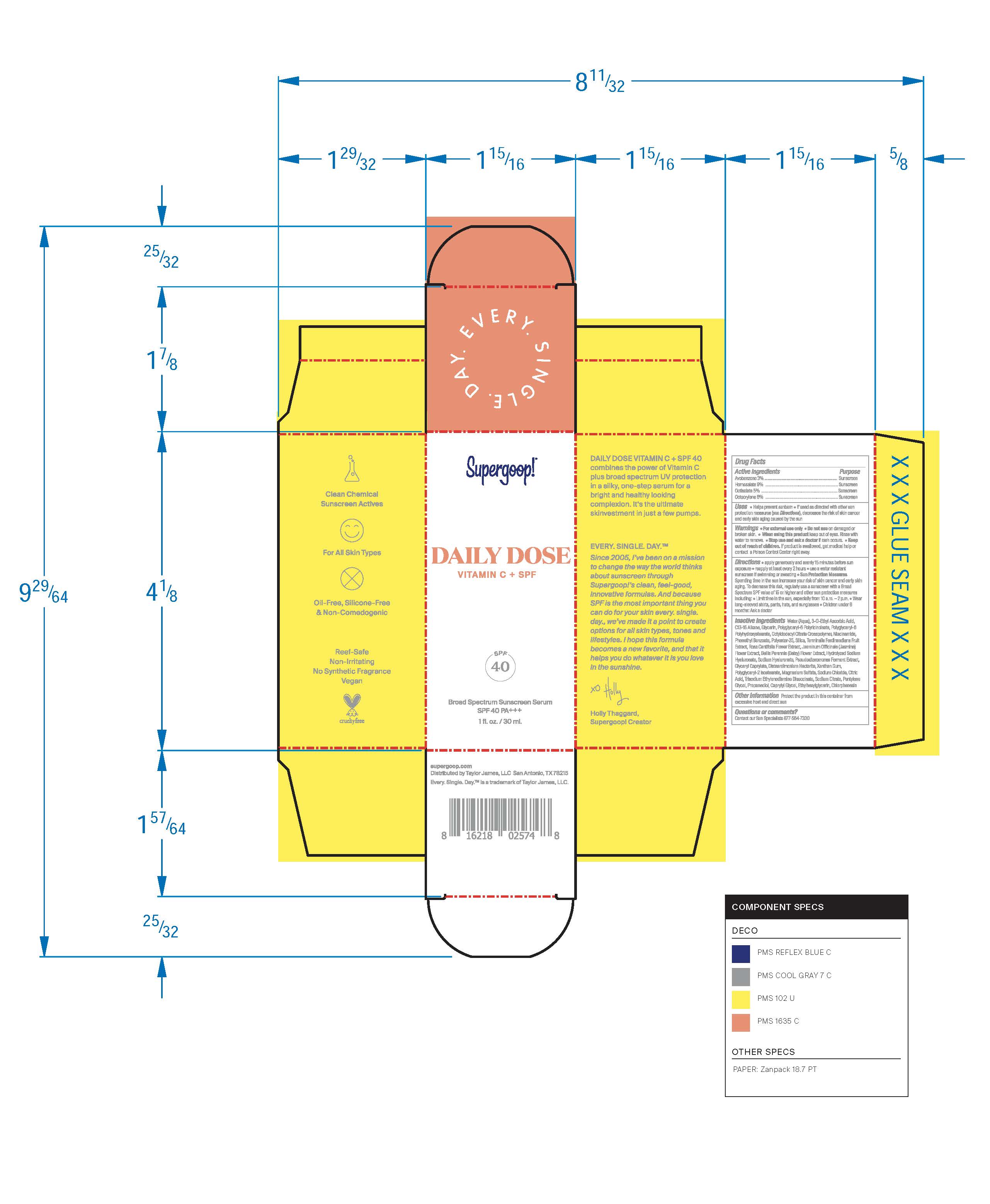 DRUG LABEL: Daily Dose Vitamin C and Broad Spectrum SPF 40 Serum
NDC: 75936-136 | Form: LOTION
Manufacturer: Supergoop LLC
Category: otc | Type: HUMAN OTC DRUG LABEL
Date: 20241204

ACTIVE INGREDIENTS: HOMOSALATE 9 g/100 mL; OCTISALATE 5 g/100 mL; AVOBENZONE 3 g/100 mL; OCTOCRYLENE 6 g/100 mL
INACTIVE INGREDIENTS: SILICON DIOXIDE; PHENETHYL BENZOATE; POLYGLYCERYL-2 ISOSTEARATE; ROSA CENTIFOLIA FLOWER; BELLIS PERENNIS FLOWER; OCTYLDODECYL CITRATE CROSSPOLYMER; HYALURONATE SODIUM; GLYCERYL MONOCAPRYLATE; 3-O-ETHYL ASCORBIC ACID; GLYCERIN; SODIUM CHLORIDE; CITRIC ACID MONOHYDRATE; KAKADU PLUM; NIACINAMIDE; CAPRYLYL GLYCOL; PENTYLENE GLYCOL; PROPANEDIOL; CHLORPHENESIN; DISTEARDIMONIUM HECTORITE; XANTHAN GUM; ETHYLHEXYLGLYCERIN; JASMINUM OFFICINALE FLOWER; MAGNESIUM SULFATE, UNSPECIFIED FORM; WATER; C13-15 ALKANE; TRISODIUM ETHYLENEDIAMINE DISUCCINATE; SODIUM CITRATE

Daily Dose Vitamin C and Broad Spectrum SPF 40 Serum

Active Ingredients Purpose

Avobenzone 3% Sunscreen

Homosalate 9% Sunscreen

Octisalate 5% Sunscreen

Octocrylene 6% Sunscreen

Uses

- Helps Prevent Sunburn
- If used as directed with other sun protection measures (see Directions), decreases the risk of skin cancer and early skin aging caused by the sun.

Keep out of reach of children. If product is swallowed, get medical help or contact a poison Control Center right away

Stop use and ask a doctor if rash occurs.

Warnings

- For external use only
- Do not use on damaged or broken skin
- When using this product keep out of eyes. Rinse with water to remove

Directions

- Apply generously and evenly 15 minutes before sun exposure
- Reapply at least every 2 hours.
- Use a water-resistant sunscreen if swimming or sweating
- Sun Protection Measures Spending time in the sun increases your risk of skin cancer and early skin aging. To decrease this risk, regularly use a sunscreen with a Broad-Spectrum SPF value of 15 or higher and other sun protection measures including:

• limit your time in the sun, especially from 10

a.m. – 2 p.m.

• wear long-sleeved shirts, pants, hats, and sunglasses •

- Children under 6 months of age: ask a doctor.

INACTIVE INGREDIENT

Inactive Ingredients Water (Aqua), 3-0-Ethyl Ascorbic Acid, C13-15 Alkane, Glycerin, Polyglyceryl-6 Ricinoleate, Polyglyceryl-6 Polyhydroxystearate, Octyldodecyl Citrate Crosspolymer, Niacinamide, Phenethyl Benzoate, Polyester-25, Silica, Terminalia Ferdinandiana Fruit Extract, Rosa Centifolia Flower Extract, Jasminum Officinale (Jasmine) Flower Extract, Bellis Perennis (Daisy) Flower Extract, Hydrolyzed sodium Hyaluronate, Sodium Hyaluronate, Pseudoalteromonas Ferment Extract, Glyceryl Caprylate, Disteardimonium Hectorite, Xanthan Gum, Polyglyceryl-2 Isostearate, Magnesium Sulfate, Sodium Chloride, Citric Acid, Trisodium Ethylenediamine Dissucinate, Sodium Citrate, Pentylene Glycol, Propanediol, Caprylyl Glycol, Ethylhexylglycerin, Chlorphenesin.

PACKAGE LABEL

Daily Dose Vitamin C + SPF

SPF 40

Broad Spectrum Serum

SPF 40 PA +++

1fl. oz. / 30 ml.